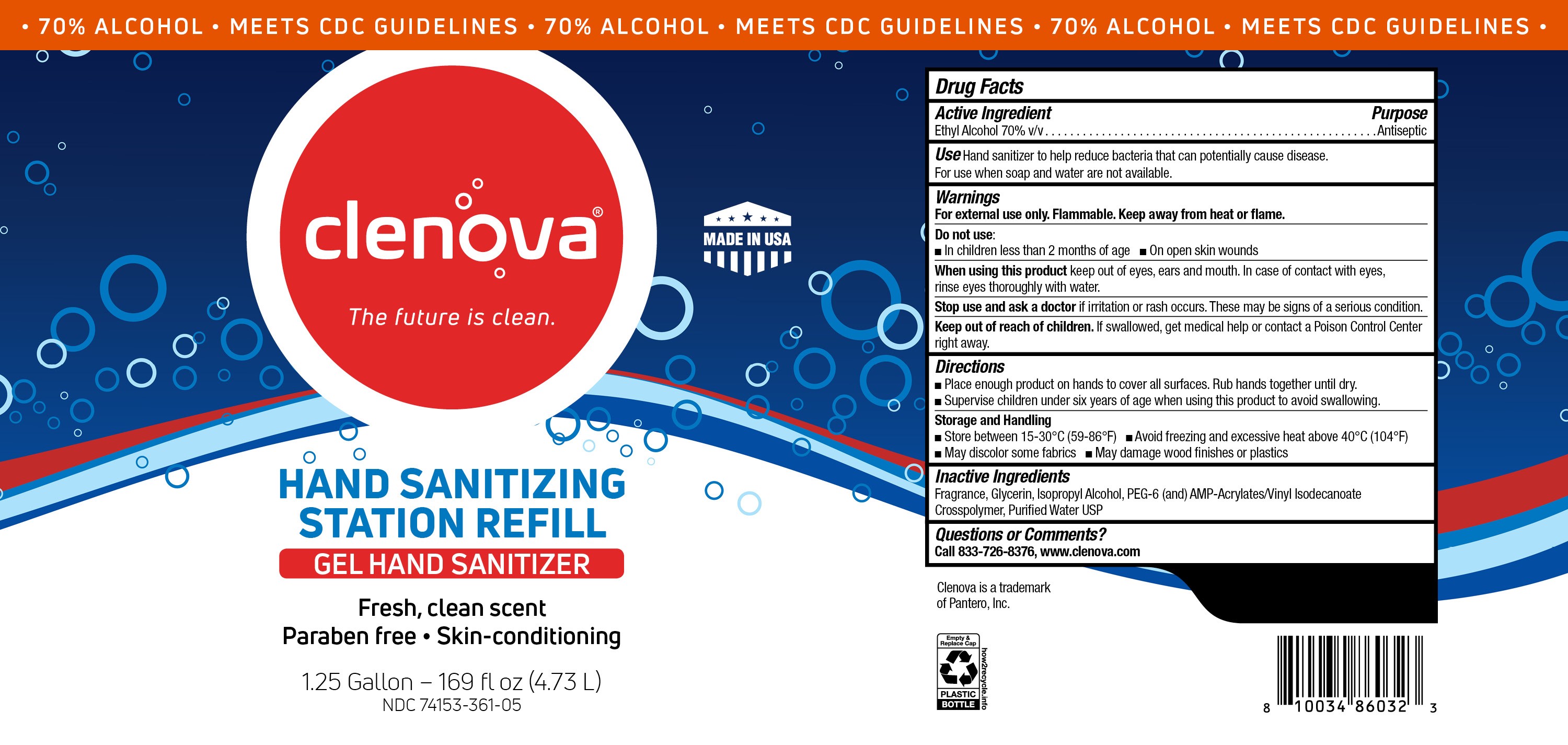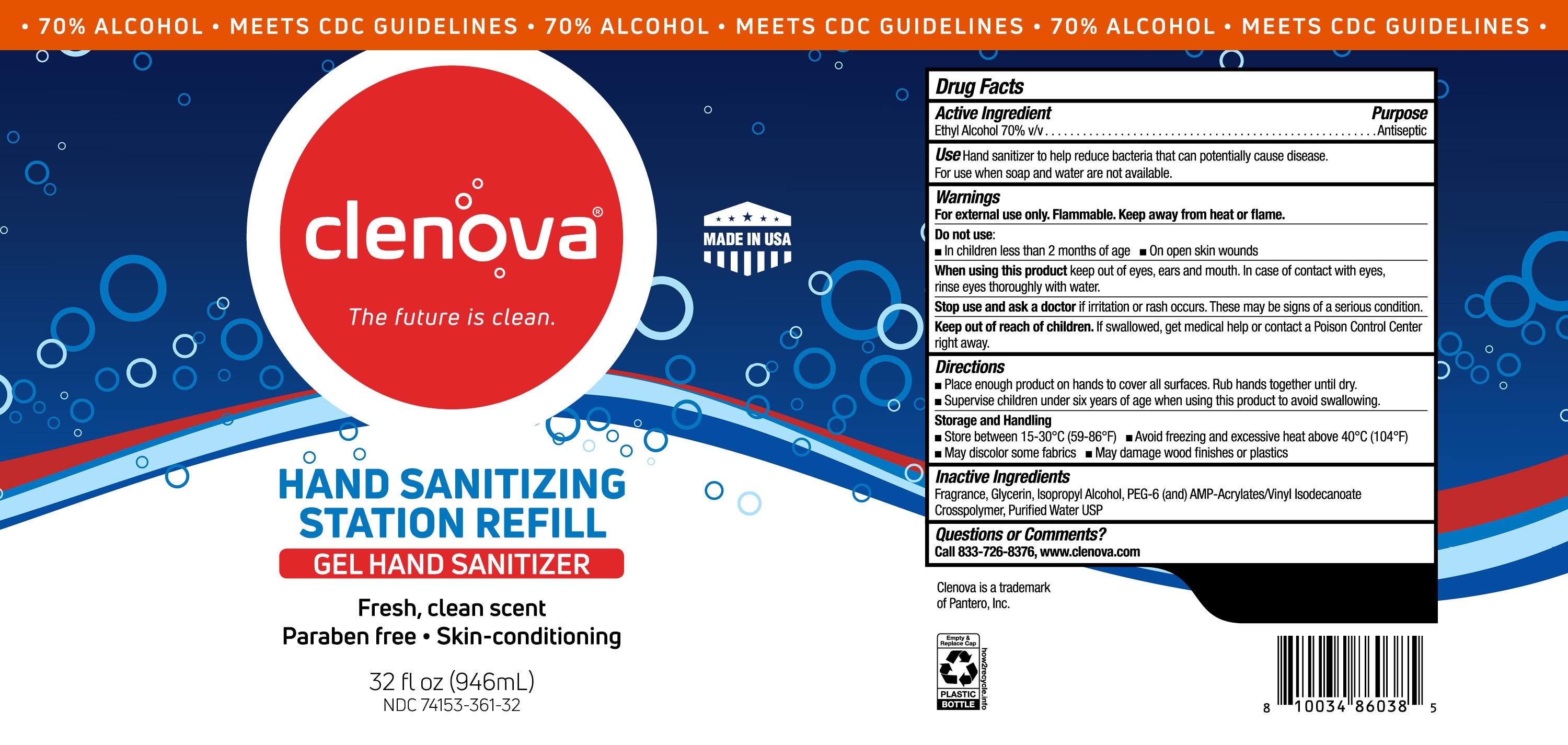 DRUG LABEL: Cleanova Gel Hand Sanitizer
NDC: 74153-361 | Form: GEL
Manufacturer: Pantero
Category: otc | Type: HUMAN OTC DRUG LABEL
Date: 20201006

ACTIVE INGREDIENTS: ALCOHOL 70 mL/100 mL
INACTIVE INGREDIENTS: ISOPROPYL ALCOHOL; GLYCERIN; RAPIDGEL EZ1; WATER

Clenova Gel Hand Sanitizer (361)

Active Ingredient(s)

Alcohol 70% v/v

Purpose

Antiseptic

Use

Hand Sanitizer to help reduce bacteria that can potentially cause disease. For use when soap and water are not available.

Warnings

For external use only. Flammable. Keep away from heat or flame

Do not use

- in children less than 2 months of age
- on open skin wounds

When using this product keep out of eyes, ears, and mouth. In case of contact with eyes, rinse eyes thoroughly with water.

Stop use and ask a doctor if irritation or rash occurs. These may be signs of a serious condition.

Keep out of reach of children. If swallowed, get medical help or contact a Poison Control Center right away.

Directions

- Place enough product on hands to cover all surfaces. Rub hands together until dry.
- Supervise children under 6 years of age when using this product to avoid swallowing.

Other information

- Store between 15-30C (59-86F)
- Avoid freezing and excessive heat above 40C (104F)
- May discolor some fabrics
- May damage wood finishes or plastics

Inactive ingredients

Fragrance, glycerin, isopropyl alcohol, PER-6 (and) AMP-acrylates/vinyl isodecanoate crosspolmer, purified water USP

Package Label - Principal Display Panel

946 mL NDC:74153-361-32

4730 mL NDC:74153-361-05